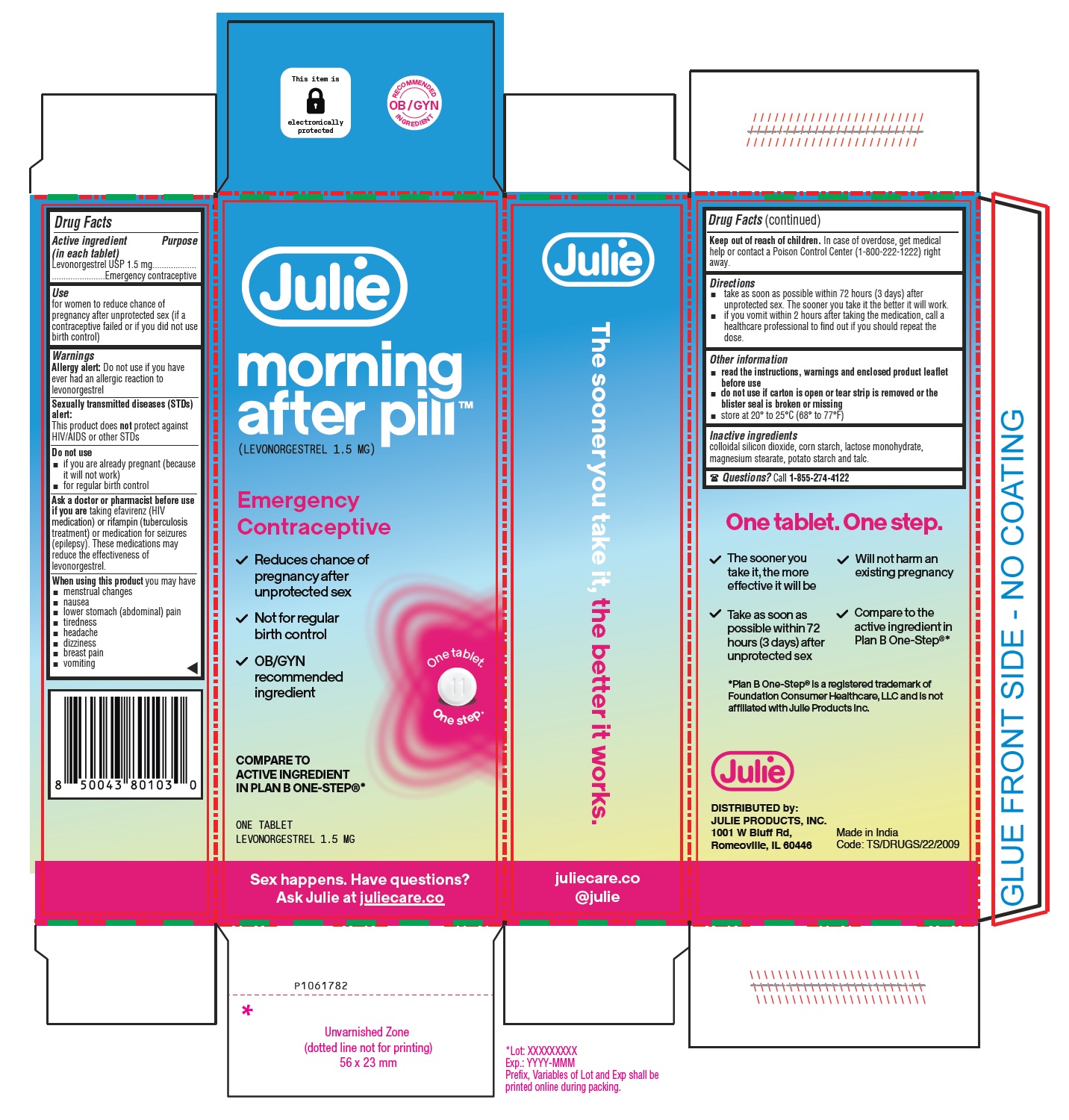 DRUG LABEL: Julie Morning After Pill
NDC: 82791-003 | Form: TABLET
Manufacturer: Julie Products Inc.
Category: otc | Type: Human OTC Drug Label
Date: 20251126

ACTIVE INGREDIENTS: LEVONORGESTREL 1.5 mg/1 1
INACTIVE INGREDIENTS: SILICON DIOXIDE; STARCH, CORN; LACTOSE MONOHYDRATE; MAGNESIUM STEARATE; STARCH, POTATO; TALC

Julie morning after pill™
(levonorgestrel tablet 1.5 mg)

Drug Facts

Active ingredient (in each tablet)
Levonorgestrel USP 1.5 mg

Purpose

Emergency contraceptive

Use

for women to reduce chance of pregnancy after unprotected sex (if a contraceptive failed or if you did not use birth control)

Warnings

Allergy alert: Do not use if you have ever had an allergic reaction to levonorgestrel
Sexually transmitted diseases (STDs) alert: This product does not protect against HIV/AIDS or other STDs

Do not use

- if you are already pregnant (because it will not work)
- for regular birth control

Ask a doctor or pharmacist before use if you are

taking efavirenz (HIV medication) or rifampin (tuberculosis treatment) or medication for seizures (epilepsy). These medications may reduce the effectiveness of levonorgestrel.

When using this product you may have

- menstrual changes
- nausea
- lower stomach (abdominal) pain
- tiredness
- headache
- dizziness
- breast pain
- vomiting

Keep out of reach of children.

In case of overdose, get medical help or contact a Poison Control Center (1-800-222-1222) right away.

Directions

- take as soon as possible within 72 hours (3 days) after unprotected sex. The sooner you take it the better it will work.
- if you vomit within 2 hours after taking the medication, call a healthcare professional to find out if you should repeat the dose.

Other information

- read the instructions, warnings and enclosed product leaflet before use
- do not use if carton is open or tear strip is removed or the blister seal is broken or missing
- store at 20° to 25°C (68° to 77°F)

Inactive ingredients

colloidal silicon dioxide, corn starch, lactose monohydrate, magnesium stearate, potato starch and talc.

Questions?

Call 1-855-274-4122

DISTRIBUTED by:
JULIE PRODUCTS, INC.
1001 W Bluff Rd,
Romeoville, IL 60446

Made in India

Code: TS/DRUGS/22/2009

Patient Information

Julie morning after pillTM

(levonorgestrel tablet 1.5 mg)

Emergency Contraceptive

One Tablet. One Step.

What You Need to Know

What is Julie morning after pillTM?

Julie morning after pillTM is emergency contraception that helps prevent pregnancy after birth control failure or unprotected sex. It is a backup method of preventing pregnancy and should not be used as regular birth control.

What Julie morning after pillTM is not.

Julie morning after pillTM will not work if you are already pregnant and will not affect an existing pregnancy. Julie morning after pillTM will not protect you from HIV infection (the virus that causes AIDS) and other sexually transmitted diseases (STDs).

When should I use Julie morning after pillTM?

The sooner you take emergency contraception, the better it works. You should use Julie morning after pillTM within 72 hours (3 days) after you have had unprotected sex.

Julie morning after pillTM is a backup or emergency method of birth control you can use when:

- your regular birth control was used incorrectly or failed
- you did not use any birth control method

When not to use Julie morning after pillTM.

Julie morning after pillTM should not be used:

- as a regular birth control method, because it’s not as effective as regular birth control.
- if you are already pregnant, because it will not work.
- if you are allergic to levonorgestrel or any other ingredients in Julie morning after pillTM.

When should I talk to a doctor or pharmacist?

Ask a doctor or pharmacist before use if you are taking efavirenz (HIV medication) or rifampin (tuberculosis treatment) or medication for seizures (epilepsy). These medications may reduce the effectiveness of Julie morning after pillTM and increase your chance of becoming pregnant. Your doctor may prescribe another form of emergency contraception that may not be affected by these medications.
How does Julie morning after pillTMwork?
Julie morning after pillTM works before release of an egg from the ovary. As a result, Julie morning after pillTM usually stops or delays the release of an egg from the ovary. Julie morning after pillTM is one tablet that contains a higher dose of levonorgestrel than birth control pills and works in a similar way to prevent pregnancy.
How can I get the best results from Julie morning after pillTM?

You have 72 hours (3 days) to try to prevent pregnancy after birth control failure or unprotected sex. The sooner you take Julie morning after pillTM, the better it works.

How effective is Julie morning after pillTM?

If Julie morning after pillTM is taken as directed, it can significantly decrease the chance that you will get pregnant. About 7 out of every 8 women who would have gotten pregnant will not become pregnant.

How will I know Julie morning after pillTM worked?

You will know Julie morning after pillTM has been effective when you get your next period, which should come at the expected time, or within a week of the expected time. If your period is delayed beyond 1 week, it is possible you may be pregnant. You should get a pregnancy test and follow up with your healthcare professional.

Will I experience any side effects?

- some women may have changes in their period, such as a period that is heavier or lighter or a period that is early or late. If your period is more than a week late, you may be pregnant.
- if you have severe abdominal pain, you may have an ectopic pregnancy, and should get immediate medical attention.
- when used as directed, Julie morning after pillTM is safe and effective. Side effects may include changes in your period, nausea, lower stomach (abdominal) pain, tiredness, headache, dizziness, and breast tenderness.
- if you vomit within 2 hours of taking the medication, call a healthcare professional to find out if you should repeat the dose.

What if I still have questions about Julie morning after pillTM ?

If you have questions or need more information, call our toll-free number AUROHEALTH LLC at 1-855-274-4122.

Other Information

Keep out of reach of children:

In case of overdose, get medical help or contact a Poison Control Center right away at 1-800-222-1222.

Do not use if the blister seal is opened.

Store at room temperature 20° to 25°C (68° to 77°F).

Active ingredient: levonorgestrel 1.5 mg

Inactive ingredients: colloidal silicon dioxide, corn starch, lactose monohydrate, magnesium stearate, potato starch, and talc.

If you are sexually active, you should see a healthcare provider for routine checkups. Your healthcare provider will talk to you about and, if necessary, test you for sexually transmitted diseases, teach you about effective methods of routine birth control, and answer any other questions you may have.

Distributed by:
JULIE PRODUCTS, INC.
1001 W Bluff Rd,
Romeoville, IL 60446
Manufactured by:
Aurobindo Pharma Limited
Hyderabad-500 032, India
Revised: 09/2025

PACKAGE LABEL-PRINCIPAL DISPLAY PANEL -1.5 mg (1 Tablet Carton Label)

Julie
morning
after pillTM

(LEVONORGESTREL 1.5 mg)
Emergency
Contraceptive
√ Reduces chance of
pregnancy after
unprotected sex
√ Not for regular
birth control

√ OB/GYN
recommended
ingredient

One tablet.
One step.

COMPARE TO
ACTIVE INGREDIENT
IN PLAN B ONE-STEP®*

ONE TABLET
LEVONORGESTREL 1.5 MG